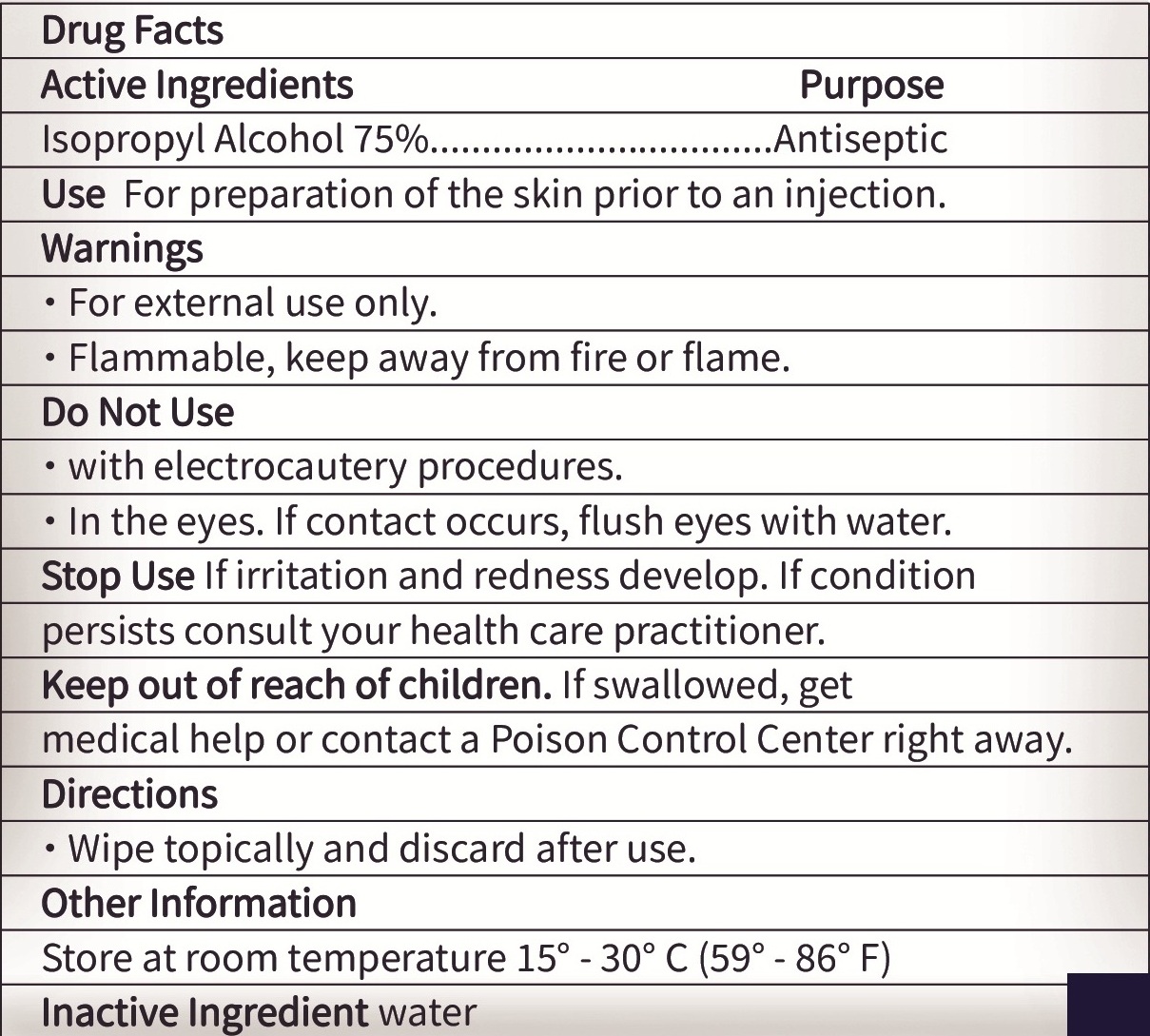 DRUG LABEL: Alcohol Prep Pads
NDC: 78149-201 | Form: SWAB
Manufacturer: Qingdao Hainuo Biological Engineering Co., Ltd.
Category: otc | Type: HUMAN OTC DRUG LABEL
Date: 20250306

ACTIVE INGREDIENTS: ISOPROPYL ALCOHOL 75 g/100 g
INACTIVE INGREDIENTS: WATER

78149-201
Alcohol Prep Pads

ACTIVE INGREDIENT

Isopropyl Alcohol 75%......................Antiseptic

INACTIVE INGREDIENT

Water

WARNINGS

- For external use only.
- Flammable, keep away from fire or flame.
- Do not use with electrocautery procedures.
- Do not use in the eyes. If contact occurs, flush eyes with water.
- Stop use if irritation and redness develop.If condition persists consult your health care parctitioner.

Keep out of reach of children. If swallowed, get medical help or contact a Poison Control Center right away

PURPOSE

For preparation of the skin prior to an injection.

INDICATIONS AND USAGE

Wipe topically and discard after use.

DOSAGE AND ADMINISTRATION

Wipe topically and discard after use.